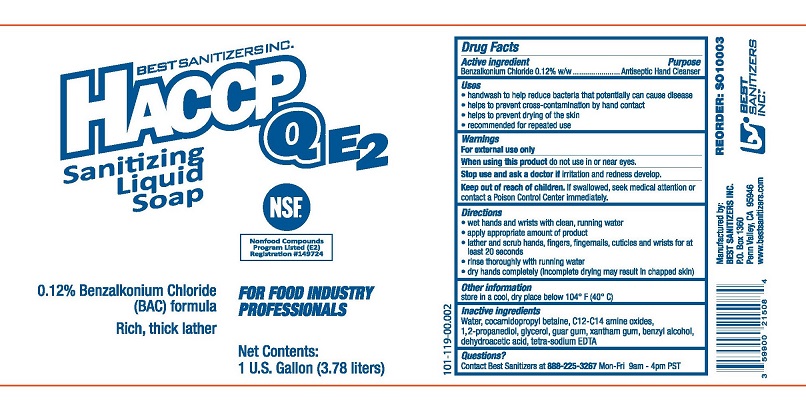 DRUG LABEL: HACCP QE2
NDC: 59900-718 | Form: LIQUID
Manufacturer: Best Sanitizers, Inc
Category: otc | Type: HUMAN OTC DRUG LABEL
Date: 20241205

ACTIVE INGREDIENTS: BENZALKONIUM CHLORIDE 1200 ug/1 mL
INACTIVE INGREDIENTS: WATER; COCAMIDOPROPYL BETAINE; PROPYLENE GLYCOL; GLYCERIN; GUAR GUM; XANTHAN GUM; BENZYL ALCOHOL; DEHYDROACETIC ACID; EDETATE SODIUM; LAURAMINE OXIDE

HACCP QE2 SANITIZING LIQUID SOAP 59900-718

Drug Facts

Active ingredient

Benzalkonium Chloride 0.12% w/w

Purpose

Antiseptic Hand Cleanser

Uses

- handwash to help reduce bacteria that potentially can cause disease
- helps to prevent cross-contamination by hand contact
- helps to prevent drying of the skin
- recommended for repeated use

Warnings

For external use only

WHEN USING

When using this productdo not use in or near eyes.

Stop use and ask a doctorif irritation and redness develop.

Keep out of reach of children.If swallowed, seek medical attention or contact a Poison Control Center immediately.

Directions

- wet hands and wrists with clean, running water
- apply appropriate amount of product
- lather and scrub hands, fingers, fingernails, cuticles and wrists for at least 20 seconds
- rinse thoroughly with running water
- dry hands completely (incomplete drying may result in chapped skin)

Other information

store in a cool dry place below 104° F (40° C)

INACTIVE INGREDIENT

Inactive ingredientsWater, cocamidopropyl betaine, C12-14 amine oxides, 1,2-propanediol, glycerol, guar gum, xanthan gum, benzyl alcohol, dehydroacetic acid, tetra-sodium EDTA

Questions?

Contact Best Sanitizers at 888-225-3267Mon-Fri 9am - 4pm PST

Manufactured by:

BEST SANITIZERS INC.

P.O. Box 1360

Penn Valley, CA 95946

www.bestsanitizers.com

PACKAGE LABEL

BEST SANITIZERS INC.

HACCP QE2

Sanitizing Liquid Soap

NSF[Nonfood Compounds Program Listed (E2) Registration #149724]

0.12% Benzalkonium Chloride (BAC) formula

Rich, thick lather

FOR FOOD INDUSTRY PROFESSIONALS

Net Contents: 1 U.S. Gallon (3.78 liters)